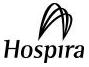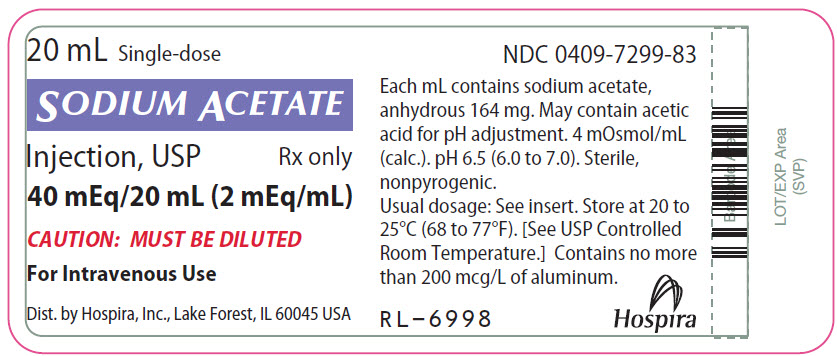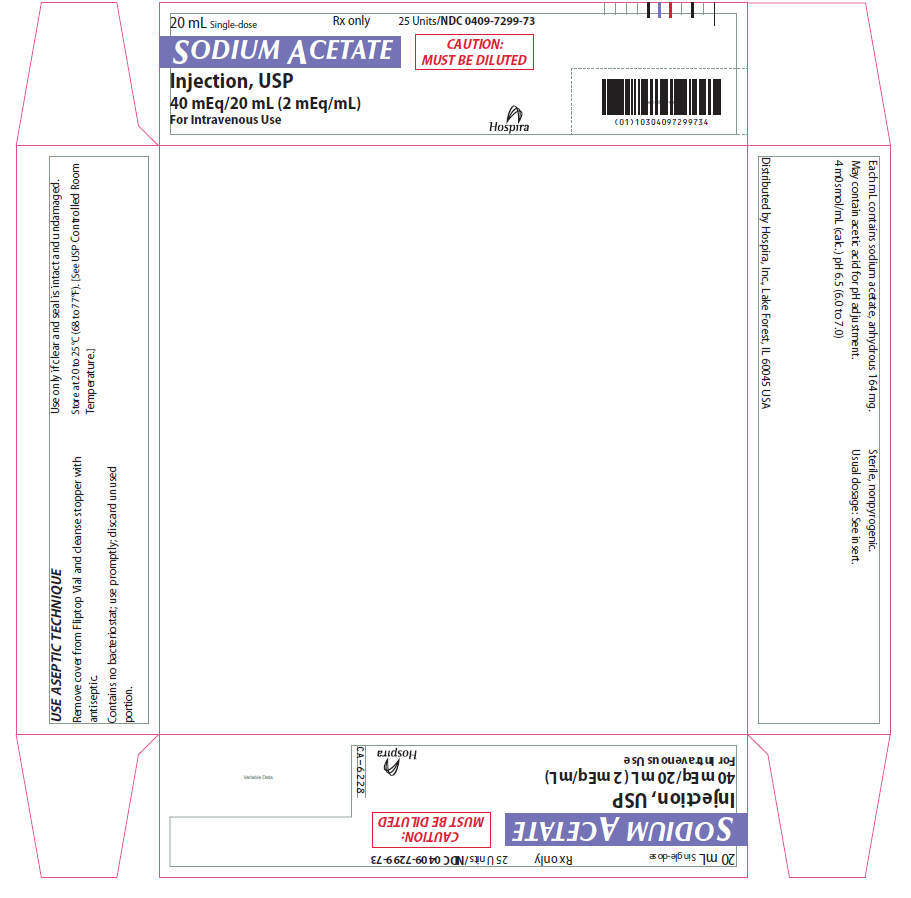 DRUG LABEL: Sodium Acetate
NDC: 0409-7299 | Form: INJECTION, SOLUTION, CONCENTRATE
Manufacturer: Hospira, Inc.
Category: prescription | Type: HUMAN PRESCRIPTION DRUG LABEL
Date: 20241120

ACTIVE INGREDIENTS: SODIUM ACETATE ANHYDROUS 3.28 g/20 mL
INACTIVE INGREDIENTS: WATER; ACETIC ACID

SODIUM ACETATE

Injection, USP

40 mEq (2 mEq/mL)

FOR ADDITIVE USE ONLY AFTER

DILUTION IN INTRAVENOUS FLUIDS.

Plastic Vial

Rx only

DESCRIPTION

Sodium Acetate Injection, USP 40 mEq (2 mEq/mL) is a sterile, nonpyrogenic, concentrated solution of sodium acetate in water for injection. The solution is administered, after dilution, by the intravenous route as an electrolyte replenisher. It must not be administered undiluted. Each 20 mL contains 3.28 g of sodium acetate (anhydrous) which provides 40 mEq each of sodium (Na^+) and acetate (CH3COO^−). The solution contains no bacteriostat, antimicrobial agent or added buffer. May contain acetic acid for pH adjustment; the pH is 6.5 (6.0 to 7.0). The osmolar concentration is 4 mOsmol/mL (calc).

The solution is intended as an alternative to sodium chloride to provide sodium ion (Na^+) for addition to large volume infusion fluids for intravenous use.

Sodium Acetate, USP (anhydrous) is chemically designated CH3COONa, a hygroscopic powder very soluble in water.

The semi-rigid container is fabricated from a specially formulated polyolefin. It is a copolymer of ethylene and propylene. The safety of the plastic has been confirmed by tests in animals according to USP biological standards for plastic containers. The container requires no vapor barrier to maintain the proper drug concentration.

CLINICAL PHARMACOLOGY

Sodium is the principal cation of extracellular fluid. It comprises more than 90% of total cations at its normal plasma concentration of approximately 140 mEq/liter. The sodium ion exerts a primary role in controlling total body water and its distribution.

Acetate (CH3COO^−), a source of hydrogen ion acceptors, is an alternate source of bicarbonate (HCO3^−) by metabolic conversion in the liver. This has been shown to proceed readily, even in the presence of severe liver disease.

INDICATIONS AND USAGE

Sodium Acetate Injection, USP 40 mEq is indicated as a source of sodium, for addition to large volume intravenous fluids to prevent or correct hyponatremia in patients with restricted or no oral intake. It is also useful as an additive for preparing specific intravenous fluid formulas when the needs of the patient cannot be met by standard electrolyte or nutrient solutions.

CONTRAINDICATIONS

Sodium Acetate Injection, USP 40 mEq is contraindicated in patients with hypernatremia or fluid retention.

WARNINGS

Sodium Acetate Injection, USP 40 mEq must be diluted before use.

To avoid sodium overload and water retention, infuse sodium-containing solutions slowly.

Solutions containing sodium ions should be used with great care, if at all, in patients with congestive heart failure, severe renal insufficiency and in clinical states in which there exists edema with sodium retention.

In patients with diminished renal function, administration of solutions containing sodium ions may result in sodium retention.

Solutions containing acetate ions should be used with great care in patients with metabolic or respiratory alkalosis. Acetate should be administered with great care in those conditions in which there is an increased level or an impaired utilization of this ion, such as severe hepatic insufficiency.

The intravenous administration of this solution (after appropriate dilution) can cause fluid and/or solute overloading resulting in dilution of other serum electrolyte concentrations, overhydration, congested states or pulmonary edema. Excessive administration of potassium free solutions may result in significant hypokalemia.

WARNING: This product contains aluminum that may be toxic. Aluminum may reach toxic levels with prolonged parenteral administration if kidney function is impaired. Premature neonates are particularly at risk because their kidneys are immature, and they require large amounts of calcium and phosphate solutions, which contain aluminum.

Research indicates that patients with impaired kidney function, including premature neonates, who receive parenteral levels of aluminum at greater than 4 to 5 mcg/kg/day accumulate aluminum at levels associated with central nervous system and bone toxicity. Tissue loading may occur at even lower rates of administration.

PRECAUTIONS

Do not administer unless solution is clear and seal is intact. Discard unused portion.

Sodium replacement therapy should be guided primarily by the serum sodium level.

Caution should be exercised in administering sodium-containing solutions to patients with severe renal function impairment, cirrhosis, cardiac failure, or other edematous or sodium-retaining states, as well as in patients with oliguria or anuria.

Caution must be exercised in the administration of parenteral fluids, especially those containing sodium ions, to patients receiving corticosteroids or corticotropin.

Solutions containing acetate ions should be used with caution as excess administration may result in metabolic alkalosis.

PREGNANCY

Pregnancy: Animal reproduction studies have not been conducted with sodium acetate. It is also not known whether sodium acetate can cause fetal harm when administered to a pregnant woman or can affect reproduction capacity. Sodium acetate should be given to a pregnant woman only if clearly needed.

PEDIATRIC USE

Pediatric Use: Safety and effectiveness have been established in the age groups infant to adolescent.

GERIATRIC USE

Geriatric Use: An evaluation of current literature revealed no clinical experience identifying differences in response between elderly and younger patients. In general, dose selection for an elderly patient should be cautious, usually starting at the low end of the dosing range, reflecting the greater frequency of decreased hepatic, renal, or cardiac function, and of concomitant disease or other drug therapy.

Sodium ions are known to be substantially excreted by the kidney, and the risk of toxic reactions may be greater in patients with impaired renal function. Because elderly patients are more likely to have decreased renal function, care should be taken in dose selection, and it may be useful to monitor renal function.

ADVERSE REACTIONS

Sodium overload can occur with intravenous infusion of excessive amounts of sodium-containing solutions. See WARNINGS and PRECAUTIONS.

OVERDOSAGE

In the event of overdosage, discontinue infusion containing sodium acetate immediately and institute corrective therapy as indicated to reduce elevated serum sodium levels, and restore acid-base balance if necessary. See WARNINGS, PRECAUTIONS and ADVERSE REACTIONS.

DOSAGE AND ADMINISTRATION

Sodium Acetate Injection, USP 40 mEq is administered intravenously only after dilution in a larger volume of fluid. The dose and rate of administration are dependent upon the individual needs of the patient. Serum sodium should be monitored as a guide to dosage. Using aseptic technique, all or part of the contents of one or more vials may be added to other intravenous fluids to provide any desired number of milliequivalents (mEq) of sodium (Na^+) with an equal number of acetate (CH3COO^−).

Parenteral drug products should be inspected visually for particulate matter and discoloration prior to administration. See PRECAUTIONS.

HOW SUPPLIED

Sodium Acetate Injection, USP 40 mEq (2 mEq/mL) is supplied as follows:

Unit of Sale | Concentration | Each
NDC 0409-7299-73 | 40 mEq/20 mL | NDC 0409-7299-83
Tray Containing 25 Units | (2 mEq/mL) | Single-dose Fliptop Vial

Each vial is partially filled to provide air space for complete vacuum withdrawal of the contents into the intravenous container.

Store at 20° to 25°C (68° to 77°F). [See USP Controlled Room Temperature.]

Distributed by
Hospira, Inc. Lake Forest, IL 60045 USA

LAB-0890-3.0

01/2018

PRINCIPAL DISPLAY PANEL - 20 mL Vial Label

20 mL Single-dose

SODIUM ACETATE

Injection, USP
Rx only

40 mEq/20 mL (2 mEq/mL)

CAUTION: MUST BE DILUTED

For Intravenous Use

Dist. by Hospira, Inc., Lake Forest, IL 60045 USA

PRINCIPAL DISPLAY PANEL - 20 mL Vial Tray

20 mL Single-dose
Rx only
25 Units/NDC 0409-7299-73

SODIUM ACETATE

Injection, USP
40 mEq/20 mL (2 mEq/mL)
For Intravenous Use

CAUTION:
MUST BE DILUTED

Hospira